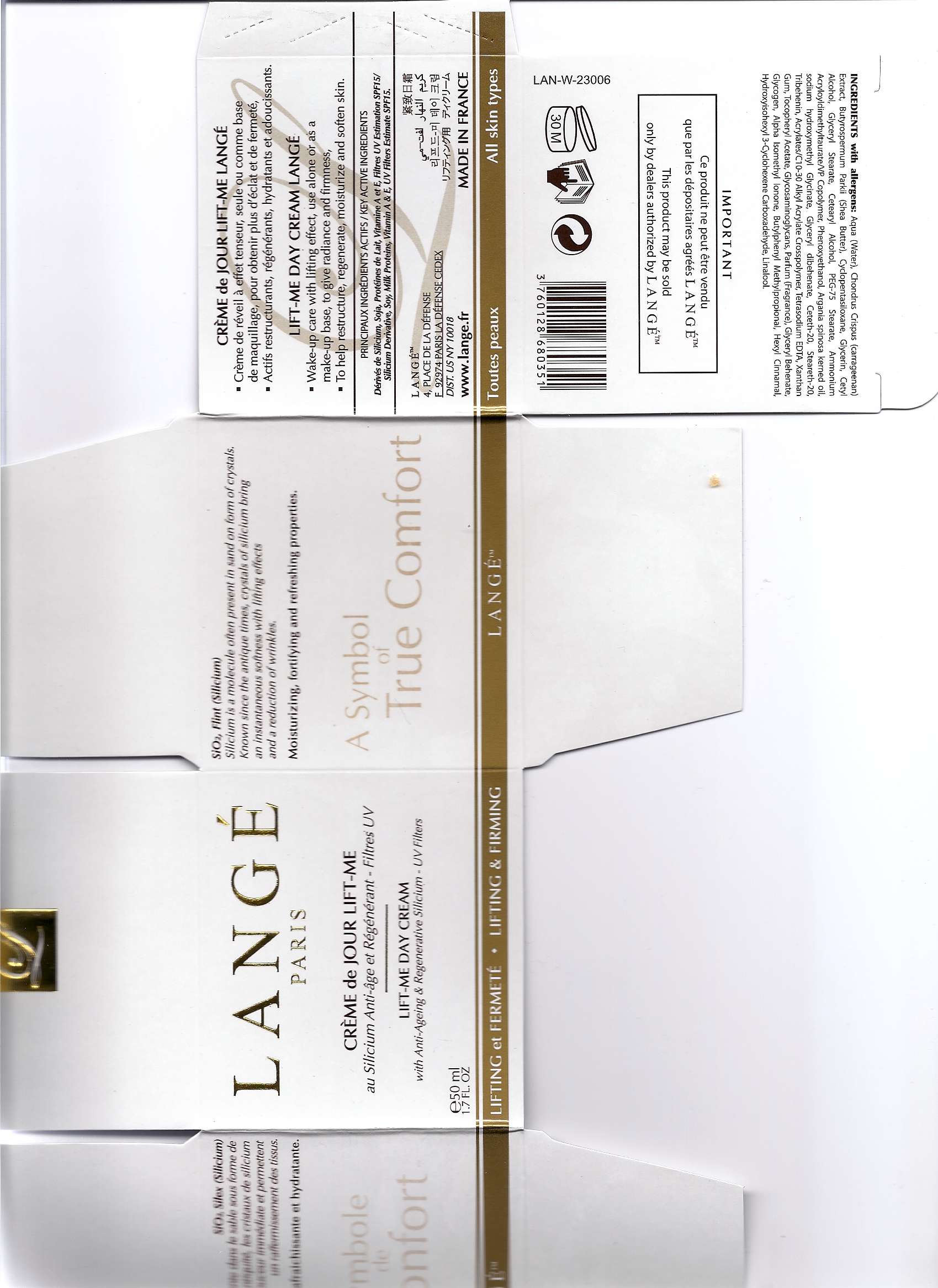 DRUG LABEL: Lift-me day cream
NDC: 51830-030 | Form: CREAM
Manufacturer: LANGE SAS
Category: otc | Type: HUMAN OTC DRUG LABEL
Date: 20100902

ACTIVE INGREDIENTS: Octinoxate 3.25 mL/50 mL; Avobenzone 1.5 mL/50 mL; Oxybenzone 1.25 mL/50 mL

Drug Facts

Active ingredients :
INCI name / USAN name
Ethylhexyl Methoxycinnamate / Octinoxate : 6,5%
Butyl Methoxydibenzoylmethane / Avobenzone : 3%
Benzophenone-3 / Oxybenzone : 2,5%
Inactive ingredients:
Aqua (water), Cyclopentasiloxane, Isononyl Isonanoate, C12-15 Alkyl Benzoate, Cetearyl Alcohol, Methylsilanol Mannuronate, Polyacrylamide, Hydrolysed Soy Protein, Glycosaminoglycans, Clyceryl Acrylate/Acrylic Acid Copolymer, Sodium Lactate, Milk Protein, Dicetyl Phosphate, C13-14 Isoparaffin, Glycerin, Glycogen, Ceteth-10 Phosphate, Laureth-7, Propylene Glycol, Helianthus Annuus (Sunflower) Seed Oil, Retinyl Palmitate, Acrylates/C10-30 Alkyl Acrylate Crosspolymer, Parfum (Fragrance), Chlorphenesin, Tocopheryl Acetate, Triclosan, Methylparaben, Propylparaben, Triethanolamine, Tetrasodium EDTA, BHT, Alpha Isomethyl Ionone, Butylphenyl Methylpropional, Citronellol, Limonene, Hexyl Cinnamal, Hydroxyisohexyl 3-Cyclohexene Carboxaldehyde, Linalool.
Directions :
- Wake-up care with lifting effect, use alone or as a make-up base, to give radiance and firmness.
- To help restructure, regenerate, moisturize and soften skin.
UV Filters estimate SPF 15

PACKAGE LABEL

MM1
Image of carton label
Lift-Me Day Cream Box 3.jpg